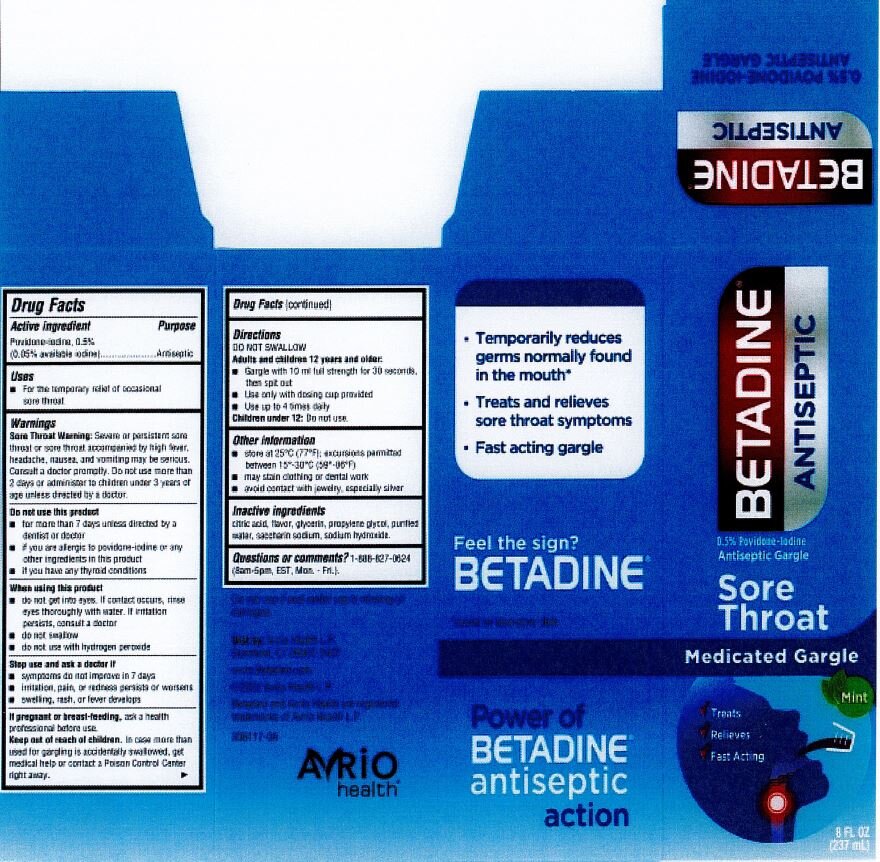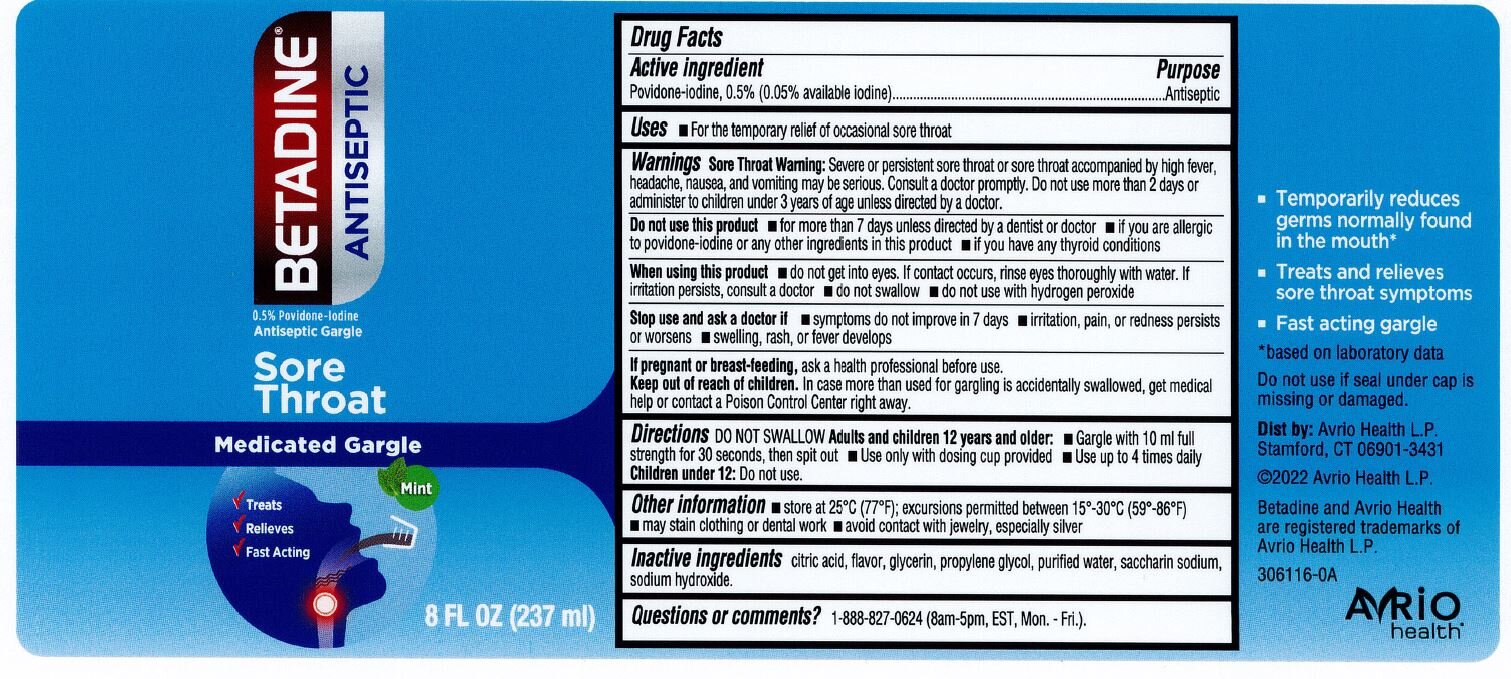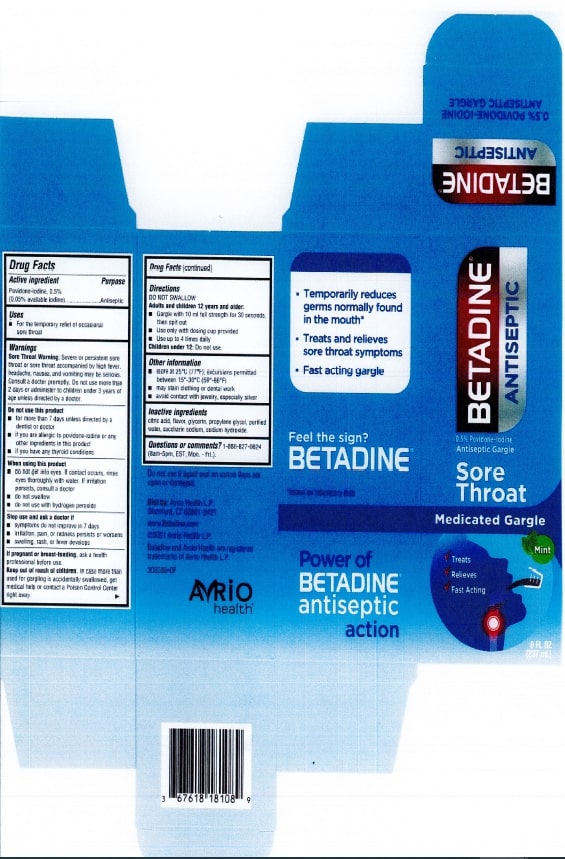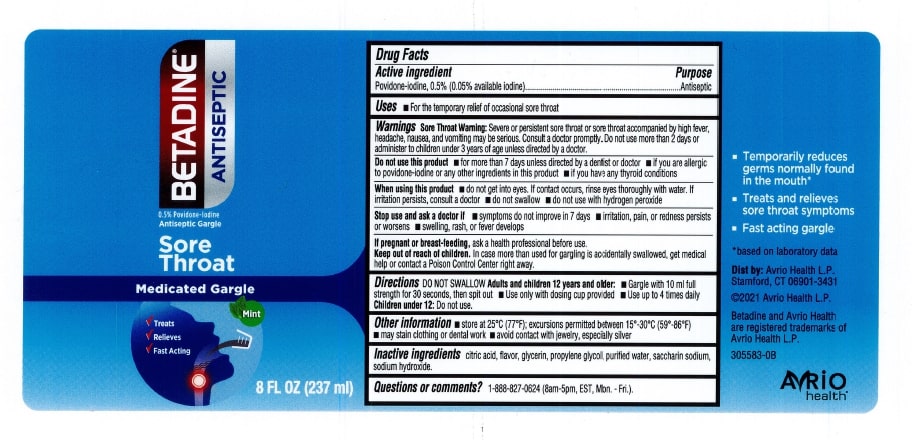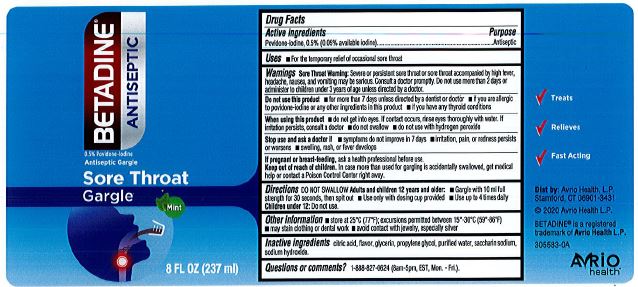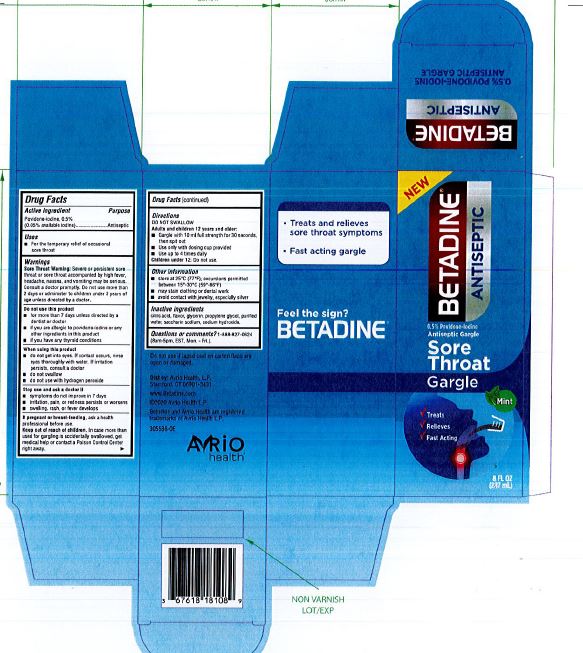 DRUG LABEL: Povidone Iodine
NDC: 82645-908 | Form: LIQUID
Manufacturer: Pharma Nobis, LLC
Category: otc | Type: HUMAN OTC DRUG LABEL
Date: 20231222

ACTIVE INGREDIENTS: POVIDONE-IODINE 5 mg/1 mL
INACTIVE INGREDIENTS: MENTHOL; SACCHARIN SODIUM; ANHYDROUS CITRIC ACID; GLYCERIN; SODIUM HYDROXIDE; WATER; PROPYLENE GLYCOL; PEPPERMINT

Private Label Povidone Iodine Gargle 0.5%

Drug Facts

Active Ingredient

Povidone-Iodine 0.5%

(0.05% available iodine)

Purpose

Antiseptic

Use

For the temporary relief of occasional sore throat.

Warnings

Severe or persistent sore throat or sore throat accompanied by high fever, headache, nausea and voniting may be serious. Consult a doctor promptly. Do not use more than 2 days or administer to children under 3 years of age unless directed by a doctor.

Stop use and consult a doctor if

Symptoms do not improve in 7 days.

Irritation, pain or redness persists or worsens.

Swelling, rash or fever develops.

When using this product do not

Get into eyes. If contact occurs, rinse eyes thoroughly with water. If iritation persists, consult a doctor.

Swallow.

Use with hydrogen peroxide.

Keep out of reach of children.

In case more than used for gargling is swallowed, get medical help or contact a Poison Control Center immediately.

Directions

DO NOT SWALLOW

Adults and children 12 years and older:

- Gargle with 10mL full strength for 30 seconds, then spit out.
- Use only with dosing cup provided.
- Use up to 4 times daily.

Children under 12:

- Do not use.

Other information

- Store at 25°C (77°F); Excursions permitted between 15°C and 30°C (59°F-86°F).
- May stain clothing or dental work.
- Avoid contact with jewelry, especially silver.

Inactive Ingredients

Citric acid, flavor, glycerin, propylene glycol, purified water, saccarin sodium, sodium hydroxide.

Do not use this product

- For more than 7 days unless directed by a dentist or doctor.
- If you are allergic to povidone-iodine or any other ingredients in this product.
- If you have any thyroid conditions.

If pregnant or breast-feeding

Ask a health professional before use.